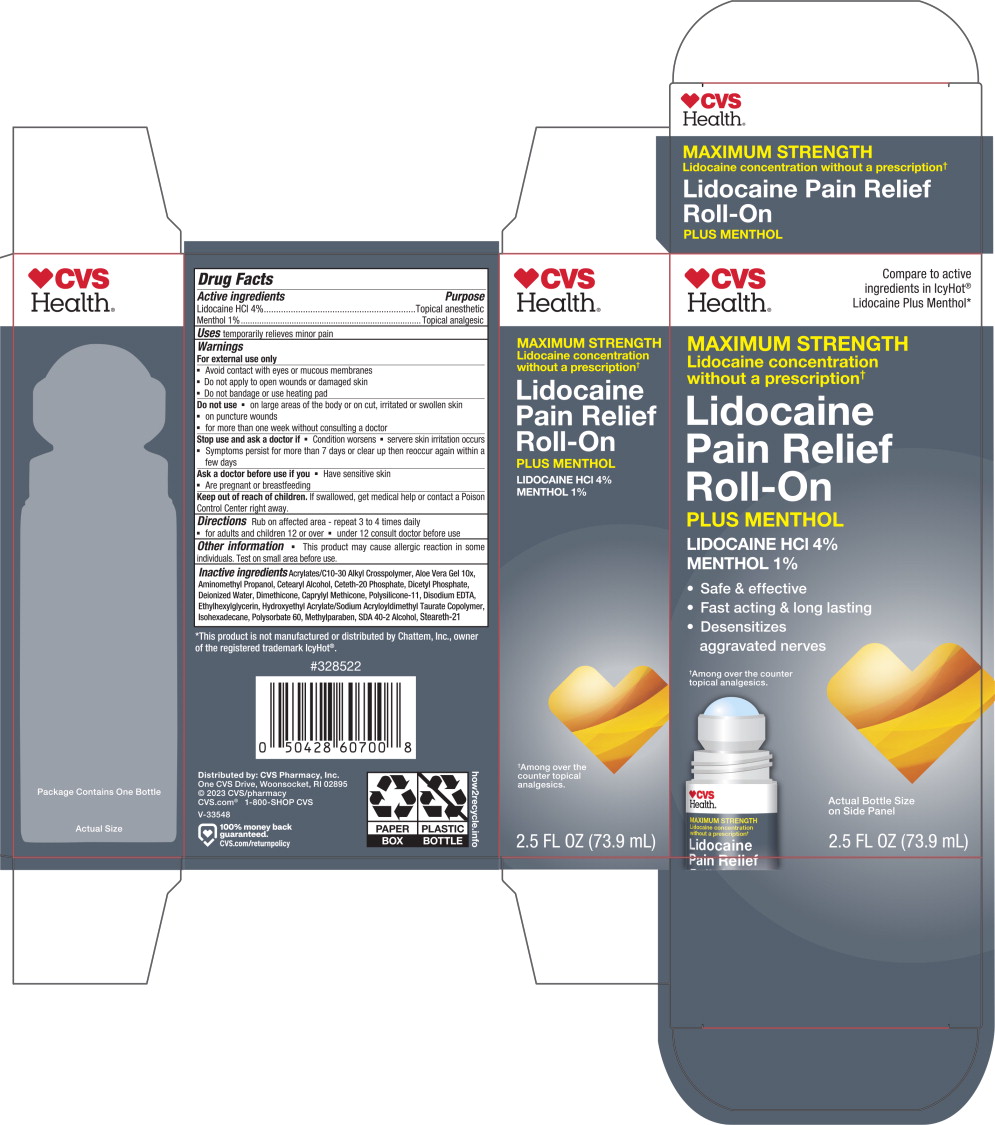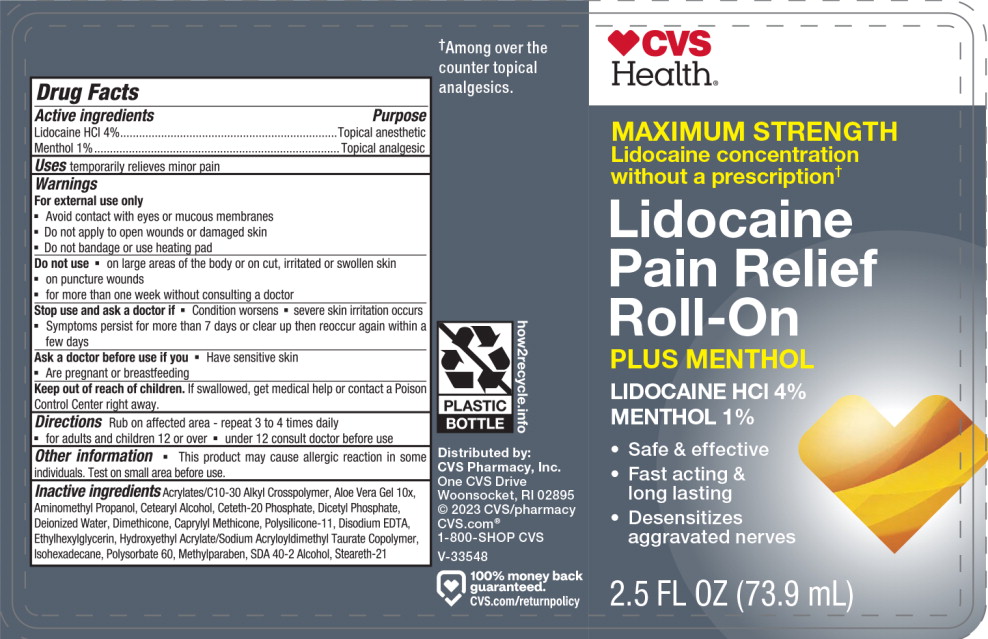 DRUG LABEL: CVS Health Cold and Hot Roll-On
NDC: 66902-156 | Form: CREAM
Manufacturer: NATURAL ESSENTIALS, INC.
Category: otc | Type: HUMAN OTC DRUG LABEL
Date: 20241004

ACTIVE INGREDIENTS: LIDOCAINE
 41 mg/1 mL; MENTHOL
 9 mg/1 mL
INACTIVE INGREDIENTS: CARBOMER COPOLYMER TYPE A; ALOE VERA LEAF; AMINOMETHYLPROPANOL; CETOSTEARYL ALCOHOL; CETETH-20 PHOSPHATE; DIHEXADECYL PHOSPHATE; WATER; DIMETHICONE; CAPRYLYL TRISILOXANE; DIMETHICONE/VINYL DIMETHICONE CROSSPOLYMER (SOFT PARTICLE); EDETATE DISODIUM; ETHYLHEXYLGLYCERIN; HYDROXYETHYL ACRYLATE/SODIUM ACRYLOYLDIMETHYL TAURATE COPOLYMER (100000 MPA.S AT 1.5%); ISOHEXADECANE; POLYSORBATE 60; METHYLPARABEN SODIUM; ALCOHOL; STEARETH-21

Drug Facts

Active ingredients

Lidocaine HCl 4%

Menthol 1%

Purpose

Topical anesthetic

Topical analgesic

Uses

temporarily relieves minor pain

Warnings

For external use only

- Avoid contact with eyes or mucous membranes
- Do not apply to open wounds or damaged skin
- Do not bandage or use heating pad

Do not use

- on large areas of the body or on cut, irritated or swollen skin
- on puncture wounds
- for more than one week without consulting a doctor

Stop use and ask a doctor if

- Condition worsens
- servere skin irritation occurs
- Symptoms persist for more than 7 days or clear up then reoccur again within a few days

Ask a doctor before use if you

- Have sensitive skin
- Are pregnant or breastfeeding

Keep out of reach of children.

If swallowed, get medical help or contact a Poison Control Center right away.

Directions

Rub on affected area - repeat 3 to 4 times daily

- for adults and children 12 or over
- under 12 consult doctor before use

Other information

- This product may cause allergic reaction in some individuals. Test on small area before use.

Inactive ingredients

Acrylates/C10-30 Alkyl Crosspolymer, Aloe Vera Gel 10x, Aminomethyl Propanol, Cetearyl Alcohol, Ceteth-20 Phosphate, Dicetyl Phosphate, Deionized Water, Dimethicone, Caprylyl Methicone, Polysilicone-11, Disodium EDTA, Ethylhexylglycerin, Hydroxyethyl Acrylate/Sodium Acryloyldimethyl Taurate Copolymer, Isohexadecane, Polysorbate 60, Methylparaben, SDA 40-2 Alcohol, Steareth-21

Principal Display Panel – 73.9 mL Carton Label

CVS
Health ®

Compare to active
ingredients in IcyHot®
Lidocaine Plus Menthol*

MAXIMUM STRENGTH

Lidocaine concentration
without a prescription ✝

Lidocaine
Pain Relief
Roll-On

PLUS MENTHOL

LIDOCAINE HCl 4%

MENTHOL 1%

- Safe & effective
- Fast acting & long lasting
- Desensitizes
  aggravated nerves

✝Among over the counter
topical analgesics.

Actual Bottle Size
on Side Panel

2.5 FL OZ (73.9 mL)

Principal Display Panel – 73.9 mL Container Label

CVS
Health ®

MAXIMUM STRENGTH

Lidocaine concentration
without a prescription ✝

Lidocaine
Pain Relief
Roll-On

PLUS MENTHOL

LIDOCAINE HCl 4%

MENTHOL 1%

- Safe & effective
- Fast acting &
  long lasting
- Desensitizes
  aggravated nerves

2.5 FL OZ (73.9 mL)